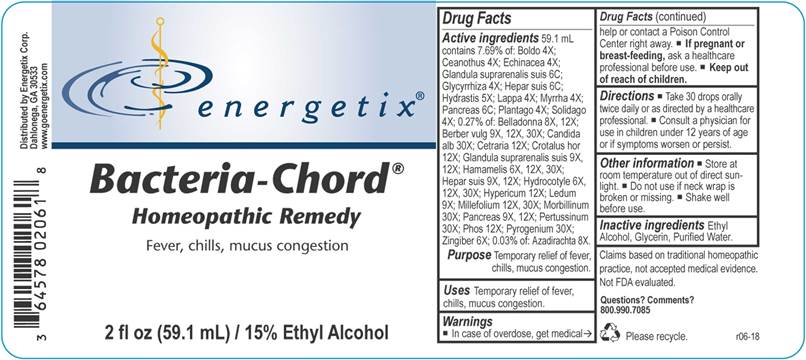 DRUG LABEL: Bacteria Chord
NDC: 64578-0131 | Form: LIQUID
Manufacturer: Energetix Corp
Category: homeopathic | Type: HUMAN OTC DRUG LABEL
Date: 20180711

ACTIVE INGREDIENTS: AZADIRACHTA INDICA BARK 8 [hp_X]/1 mL; ATROPA BELLADONNA 8 [hp_X]/1 mL; BERBERIS VULGARIS ROOT BARK 9 [hp_X]/1 mL; PEUMUS BOLDUS LEAF 4 [hp_X]/1 mL; CANDIDA ALBICANS 30 [hp_X]/1 mL; CEANOTHUS AMERICANUS LEAF 4 [hp_X]/1 mL; CETRARIA ISLANDICA SUBSP. ISLANDICA 12 [hp_X]/1 mL; CROTALUS HORRIDUS HORRIDUS VENOM 12 [hp_X]/1 mL; ECHINACEA ANGUSTIFOLIA 4 [hp_X]/1 mL; SUS SCROFA ADRENAL GLAND 9 [hp_X]/1 mL; GLYCYRRHIZA GLABRA 4 [hp_X]/1 mL; HAMAMELIS VIRGINIANA ROOT BARK/STEM BARK 6 [hp_X]/1 mL; PORK LIVER 9 [hp_X]/1 mL; GOLDENSEAL 5 [hp_X]/1 mL; CENTELLA ASIATICA 6 [hp_X]/1 mL; HYPERICUM PERFORATUM 12 [hp_X]/1 mL; ARCTIUM LAPPA ROOT 4 [hp_X]/1 mL; LEDUM PALUSTRE TWIG 9 [hp_X]/1 mL; ACHILLEA MILLEFOLIUM 12 [hp_X]/1 mL; MEASLES VIRUS 30 [hp_X]/1 mL; MYRRH 4 [hp_X]/1 mL; SUS SCROFA PANCREAS 9 [hp_X]/1 mL; HUMAN SPUTUM, BORDETELLA PERTUSSIS INFECTED 30 [hp_X]/1 mL; PHOSPHORUS 12 [hp_X]/1 mL; PLANTAGO MAJOR 4 [hp_X]/1 mL; RANCID BEEF 30 [hp_X]/1 mL; SOLIDAGO VIRGAUREA FLOWERING TOP 4 [hp_X]/1 mL; GINGER 6 [hp_X]/1 mL
INACTIVE INGREDIENTS: WATER; ALCOHOL

Drug Facts:

ACTIVE INGREDIENTS:

59.1 mL contains 7.69% of: Boldo 4X; Ceanothus Americanus 4X; Echinacea (Angustifolia) 4X; Glandula Suprarenalis Suis 6C, Glycyrrhiza Glabra 4X; Hepar Suis 6C; Hydrastis Canadensis 5X; Lappa Major 4X; Myrrha 4X; Pancreas Suis 6C; Plantago Major 4X; Solidago Virgaurea 4X; 0.27% of: Belladonna 8X, 12X; Candida Albicans 30X; Cetraria Islandica 12X; Crotalus Horridus 12X; Glandula Suprarenalis Suis 9X, 12X; Hamamelis Virginiana 6X, 12X, 30X; Hepar Suis 9X, 12X; Hydrocotyle Asiatica 6X, 12X, 30X; Hypericum Perforatum 12X; Ledum Palustre 9X, Millefolium 12X, 30X, Morbillinum 30X, Pancreas Suis 9X, 12X; Pertussinum 30X, Phosphorus 12X, Pyrogenium 30X, Zingiber Officinale 6X; 0.03% of: Azadirachta Indica 8X.

PURPOSE:

Temporary relief of fever, chills, mucus congestion.

Claims based on traditional homeopathic practice, not accepted medical evidence. Not FDA evaluated.

WARNINGS:

In case of overdose, get medical help or contact a Poison Control Center right away.

If pregnant or breast feeding, ask a health professional before use.

Keep out of reach of children.

Keep out of reach of children. In case of overdose, get medical help or contact a Poison Control Center right away.

DIRECTIONS

Take 30 drops orally twice daily or as directed by a healthcare professional.
Consult a physician for use in children under 12 years of age or if symptoms worsen or persist.

USES:

Temporary relief of fever, chills, mucus congestion.

Claims based on traditional homeopathic practice, not accepted medical evidence. Not FDA evaluated.

INACTIVE INGREDIENTS:

Ethyl Alcohol, Glycerin, Purified Water

QUESTIONS:

Distributed by
Energetix Corp.
Dahlonega, GA 30533
Questions: 800.990.7085
www.goenergetix.com

PACKAGE LABEL DISPLAY:

energetix
Bacteria-Chord
Homeopathic Remedy
Fever, chills, mucus congestion
2 fl oz (59.1 mL)